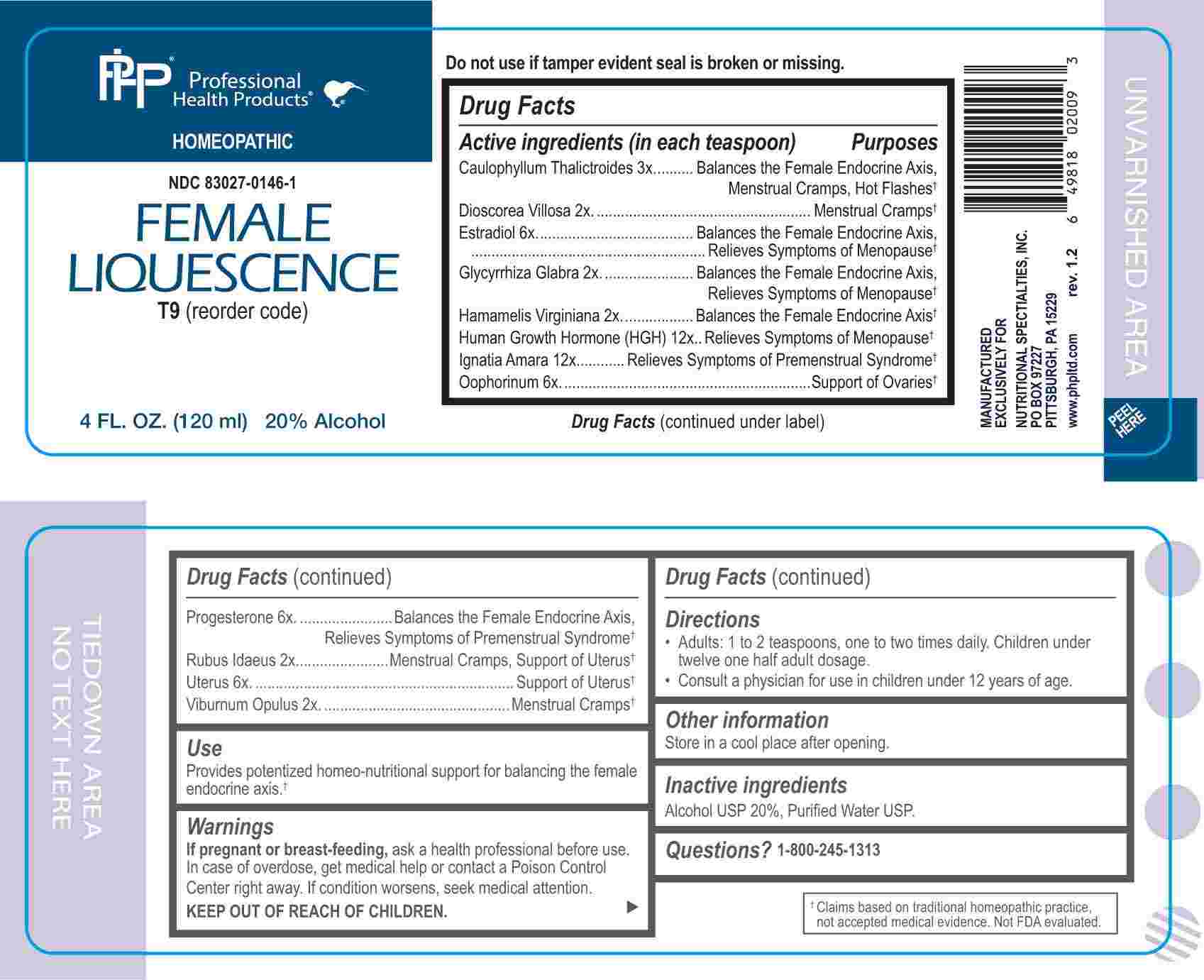 DRUG LABEL: Female Liquescence
NDC: 83027-0146 | Form: LIQUID
Manufacturer: Nutritional Specialties, Inc.
Category: homeopathic | Type: HUMAN OTC DRUG LABEL
Date: 20240925

ACTIVE INGREDIENTS: DIOSCOREA VILLOSA TUBER 2 [hp_X]/1 mL; GLYCYRRHIZA GLABRA 2 [hp_X]/1 mL; HAMAMELIS VIRGINIANA ROOT BARK/STEM BARK 2 [hp_X]/1 mL; RUBUS IDAEUS LEAF 2 [hp_X]/1 mL; VIBURNUM OPULUS BARK 2 [hp_X]/1 mL; CAULOPHYLLUM THALICTROIDES ROOT 3 [hp_X]/1 mL; ESTRADIOL 6 [hp_X]/1 mL; SUS SCROFA OVARY 6 [hp_X]/1 mL; PROGESTERONE 6 [hp_X]/1 mL; SUS SCROFA UTERUS 6 [hp_X]/1 mL; SOMATROPIN 12 [hp_X]/1 mL; STRYCHNOS IGNATII SEED 12 [hp_X]/1 mL
INACTIVE INGREDIENTS: WATER; ALCOHOL

DRUG FACTS:

ACTIVE INGREDIENTS:

(in each teaspoon) Caulophyllum Thalictroides 3X, Dioscorea Villosa 2X, Estradiol 6X, Glycyrrhiza Glabra 2X, Hamamelis Virginiana 2X, Human Growth Hormone (HGH) 12X, Ignatia Amara 12X, Oophorinum 6X, Progesterone 6X, Rubus Idaeus 2X, Uterus 6X, Viburnum Opulus 2X.

PURPOSE:

Caulophyllum Thalictroides – Balances the Female Endocrine Axis,† Menstrual Cramps, Hot Flashes, Dioscorea Villosa – Menstrual Cramps,† Estradiol – Balances the Female Endocrine Axis, Relieves Symptoms of Menopause,† Glycyrrhiza Glabra - Balances the Female Endocrine Axis, Relieves Symptoms of Menopause,† Hamamelis Virginiana - Balances the Female Endocrine Axis,† Human Growth Hormone (HGH) – Relieves Symptoms of Menopause,† Ignatia Amara – Relieves Symptoms of Premenstrual Syndrome,† Oophorinum – Support of Ovaries,† Progesterone – Balances the Female Endocrine Axis, Relieves Symptoms of Premenstrual Syndrome,† Rubus Idaeus – Menstrual Cramps, Support of Uterus,† Uterus – Support of Uterus,† Viburnum Opulus – Menstrual Cramps†

USES:

Provides potentized homeo-nutritional support for balancing the female endocrine axis.†

†Claims based on traditional homeopathic practice, not accepted medical evidence. Not FDA evaluated.

WARNINGS:

If pregnant or breast-feeding, ask a health professional before use.

In case of overdose, get medical help or contact a Poison Control Center right away.

If condition worsens, seek medical attention.

KEEP OUT OF REACH OF CHILDREN

Do not use if tamper evident seal is broken or missing.

Store in a cool place after opening

KEEP OUT OF REACH OF CHILDREN:

In case of overdose, get medical help or contact a Poison Control Center right away.

DIRECTIONS:

• Adults: 1 to 2 teaspoons, one to two times daily. Children under twelve one half adult dosage.

Consult a physician for use in children under 12 years of age.

INACTIVE INGREDIENTS:

Alcohol USP 20%, Purified Water USP.

QUESTIONS:

MANUFACTURED EXCLUSIVELY FOR

NUTRITIONAL SPECIALTIES, INC.

PO BOX 97227

PITTSBURG, PA 15229

www.phpltd.com

1-800-245-1313

PACKAGE LABEL DISPLAY:

Professional

Health Products

HOMEOPATHIC

NDC 83027-0146-1

FEMALE LIQUESCENCE

4 FL. OZ (120 ml)